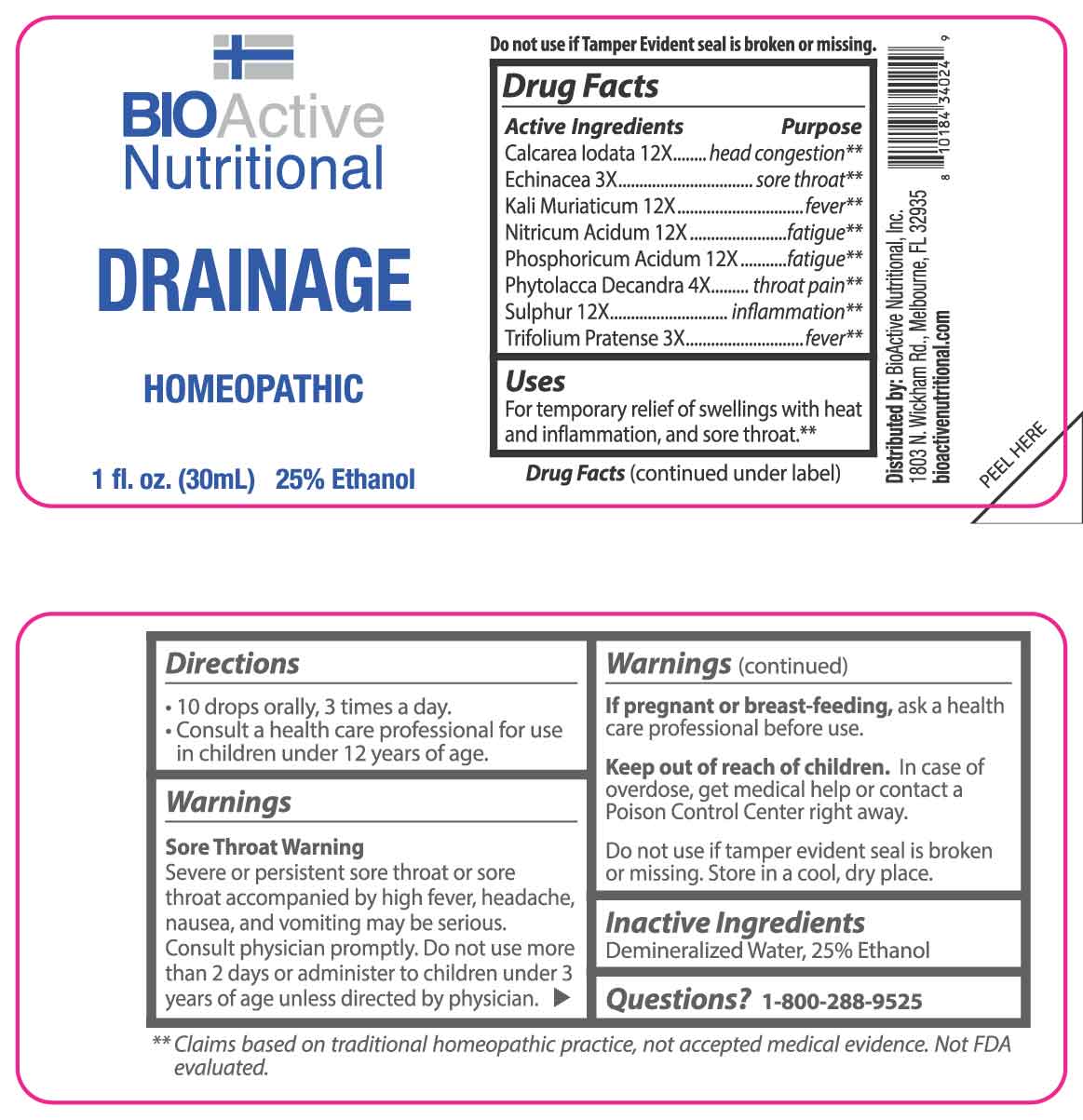 DRUG LABEL: Drainage
NDC: 43857-0642 | Form: LIQUID
Manufacturer: BioActive Nutritional, Inc.
Category: homeopathic | Type: HUMAN OTC DRUG LABEL
Date: 20250520

ACTIVE INGREDIENTS: ECHINACEA ANGUSTIFOLIA WHOLE 3 [hp_X]/1 mL; TRIFOLIUM PRATENSE FLOWER 3 [hp_X]/1 mL; PHYTOLACCA AMERICANA ROOT 4 [hp_X]/1 mL; CALCIUM IODIDE 12 [hp_X]/1 mL; POTASSIUM CHLORIDE 12 [hp_X]/1 mL; NITRIC ACID 12 [hp_X]/1 mL; PHOSPHORIC ACID 12 [hp_X]/1 mL; SULFUR 12 [hp_X]/1 mL
INACTIVE INGREDIENTS: WATER; ALCOHOL

DRUG FACTS:

ACTIVE INGREDIENTS:

Calcarea Iodata 12X, Echinacea 3X, Kali Muriaticum 12X, Nitricum Acidum 12X, Phosphoricum Acidum 12X, Phytolacca Decandra 4X, Sulphur 12X, Trifolium Pratense 3X.

PURPOSE:

Calcarea Iodata – head congestion,** Echinacea – sore throat,** Kali Muriaticum - fever,** Nitricum Acidum - fatigue,** Phosphoricum Acidum - fatigue,** Phytolacca Decandra – throat pain,** Sulphur - inflammation,** Trifolium Pratense – fever**

**Claims based on traditional homeopathic practice, not accepted medical evidence. Not FDA evaluated.

USES:

For temporary relief of swellings with heat and inflammation, and sore throat.**

**Claims based on traditional homeopathic practice, not accepted medical evidence. Not FDA evaluated.

WARNINGS:

Sore Throat Warning

Severe or persistent sore throat or sore throat accompanied by high fever, headache, nausea, and vomiting may be serious. Consult physician promptly. Do not use more than 2 days or administer to children under 3 years of age unless directed by physician.

If pregnant or breast-feeding, ask a health care professional before use.

Keep out of reach of children. In case of overdose, get medical help or contact a Poison Control Center right away.

Do not use if tamper evident seal is broken or missing.

Store in a cool, dry place.

KEEP OUT OF REACH OF CHILDREN:

In case of overdose, get medical help or contact a Poison Control Center right away.

DIRECTIONS:

• 10 drops orally, 3 times a day.

• Consult a health care professional for use in children under 12 years of age.

INACTIVE INGREDIENTS:

Demineralized Water, 25% Ethanol

QUESTIONS:

Distributed by:
BioActive Nutritional, Inc.
1803 N. Wickham Rd.
Melbourne, FL 32935
bioactivenutritional.com

1-800-288-9525

PACKAGE LABEL DISPLAY:

BIOActiveNutritional

DRAINAGE

HOMEOPATHIC

1 fl. oz. (30mL)